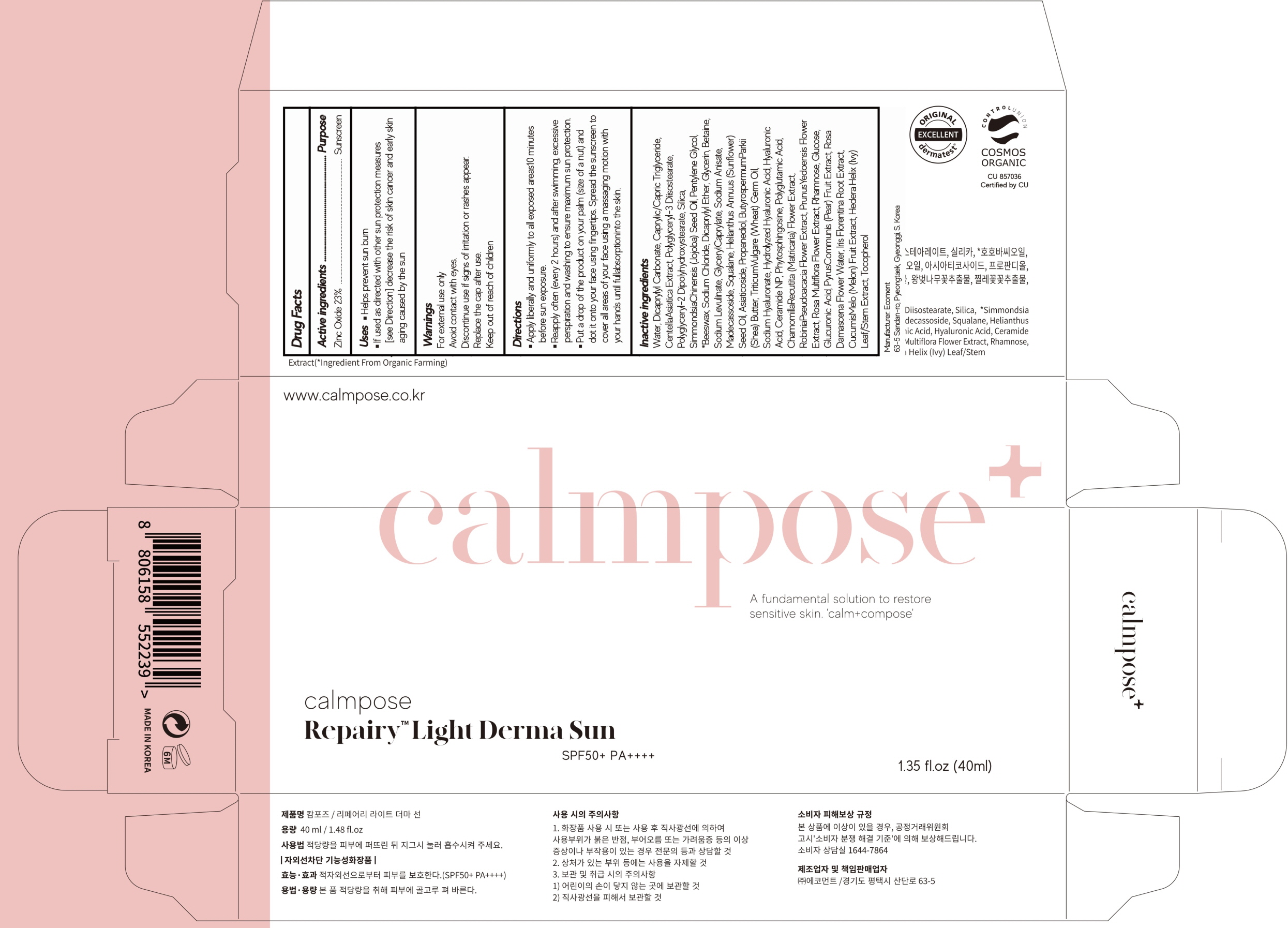 DRUG LABEL: calmpose Repairy Light Derma Sun
NDC: 78958-010 | Form: CREAM
Manufacturer: Ecoment
Category: otc | Type: HUMAN OTC DRUG LABEL
Date: 20201030

ACTIVE INGREDIENTS: Zinc Oxide 9.2 g/40 mL
INACTIVE INGREDIENTS: Water; Dicaprylyl Carbonate; MEDIUM-CHAIN TRIGLYCERIDES

ACTIVE INGREDIENT

Zinc Oxide 23%

INACTIVE INGREDIENTS

Water, Dicaprylyl Carbonate, Caprylic/Capric Triglyceride, CentellaAsiatica Extract, Polyglyceryl-3 Diisostearate, Polyglyceryl-2 Dipolyhydroxystearate, Silica, SimmondsiaChinensis (Jojoba) Seed Oil, Pentylene Glycol, *Beeswax, Sodium Chloride, Dicaprylyl Ether, Glycerin, Betaine, Sodium Levulinate, GlycerylCaprylate, Sodium Anisate, Madecassoside, Squalane, Helianthus Annuus (Sunflower) Seed Oil, Asiaticoside, Propanediol, ButyrospermumParkii (Shea) Butter, TriticumVulgare (Wheat) Germ Oil, Sodium Hyaluronate, Hydrolyzed Hyaluronic Acid, Hyaluronic Acid, Ceramide NP, Phytosphingosine, Polyglutamic Acid, ChamomillaRecutita (Matricaria) Flower Extract, RobiniaPseudoacacia Flower Extract, PrunusYedoensis Flower Extract, Rosa Multiflora Flower Extract, Rhamnose, Glucose, Glucuronic Acid, PyrusCommunis (Pear) Fruit Extract, Rosa Damascena Flower Water, Iris Florentina Root Extract, CucumisMelo (Melon) Fruit Extract, Hedera Helix (Ivy) Leaf/Stem Extract, Tocopherol

PURPOSE

Sunscreen

WARNINGS

For external use only
Avoid contact with eyes.
Discontinue use if signs of irritation or rashes appear.
Replace the cap after use.
Keep out of reach of children

Uses

■ Helps prevent sun burn
■ If used as directed with other sun protection measures [see Direction] decrease the risk of skin cancer and early skin aging caused by the sun

Directions

■ Apply liberally and uniformly to all exposed areas10 minutes before sun exposure.
■ Reapply often (every 2 hours) and after swimming, excessive perspiration and washing to ensure maximum sun protection.
■ Put a drop of the product on your palm (size of a nut) and dot it onto your face using fingertips. Spread the sunscreen to cover all areas of your face using a massaging motion with your hands until full absorption into the skin.